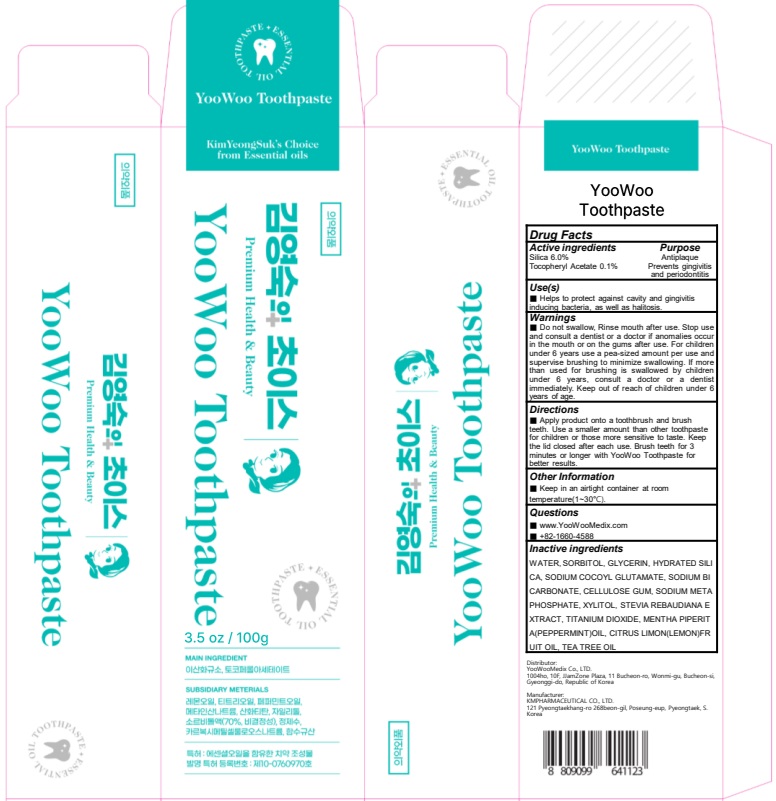 DRUG LABEL: YooWoo Tooth
NDC: 84875-010 | Form: PASTE, DENTIFRICE
Manufacturer: YOOWOOMEDIX
Category: otc | Type: HUMAN OTC DRUG LABEL
Date: 20241030

ACTIVE INGREDIENTS: .ALPHA.-TOCOPHEROL ACETATE 0.1 g/100 g; SILICON DIOXIDE 6 g/100 g
INACTIVE INGREDIENTS: SORBITOL; HYDRATED SILICA; WATER; GLYCERIN

ACTIVE INGREDIENT

Silica 6.0%

Tocopheryl Acetate 0.1%

INACTIVE INGREDIENT

WATER, SORBITOL, GLYCERIN, HYDRATED SILICA, SODIUM COCOYL GLUTAMATE, SODIUM BICARBONATE, CELLULOSE GUM, SODIUM METAPHOSPHATE, XYLITOL, STEVIA REBAUDIANA EXTRACT, TITANIUM DIOXIDE, MENTHA PIPERITA(PEPPERMINT)OIL, CITRUS LIMON(LEMON)FRUIT OIL, TEA TREE OIL

PURPOSE

Antiplaque

Prevents gingivitis and periodontitis

WARNINGS

■ Do not swallow, Rinse mouth after use. Stop use and consult a dentist or a doctor if anomalies occur in the mouth or on the gums after use. For children under 6 years use a pea-sized amount per use and supervise brushing to minimize swallowing. If more than used for brushing is swallowed by children under 6 years, consult a doctor or a dentist immediately. Keep out of reach of children under 6 years of age.

Keep out of reach of children under 6 years of age.

INDICATIONS AND USAGE

Use(s)

■ Helps to protect against cavity and gingivitis inducing bacteria, as well as halitosis.

Directions

■ Apply product onto a toothbrush and brush teeth. Use a smaller amount than other toothpaste for children or those more sensitive to taste. Keep the lid closed after each use. Brush teeth for 3 minutes or longer with YooWoo Toothpaste for better results.

Other Information

■ Keep in an airtight container at room temperature(1~30°C).

QUESTIONS

■ www.YooWooMedix.com

■ 82-2-1660-4588